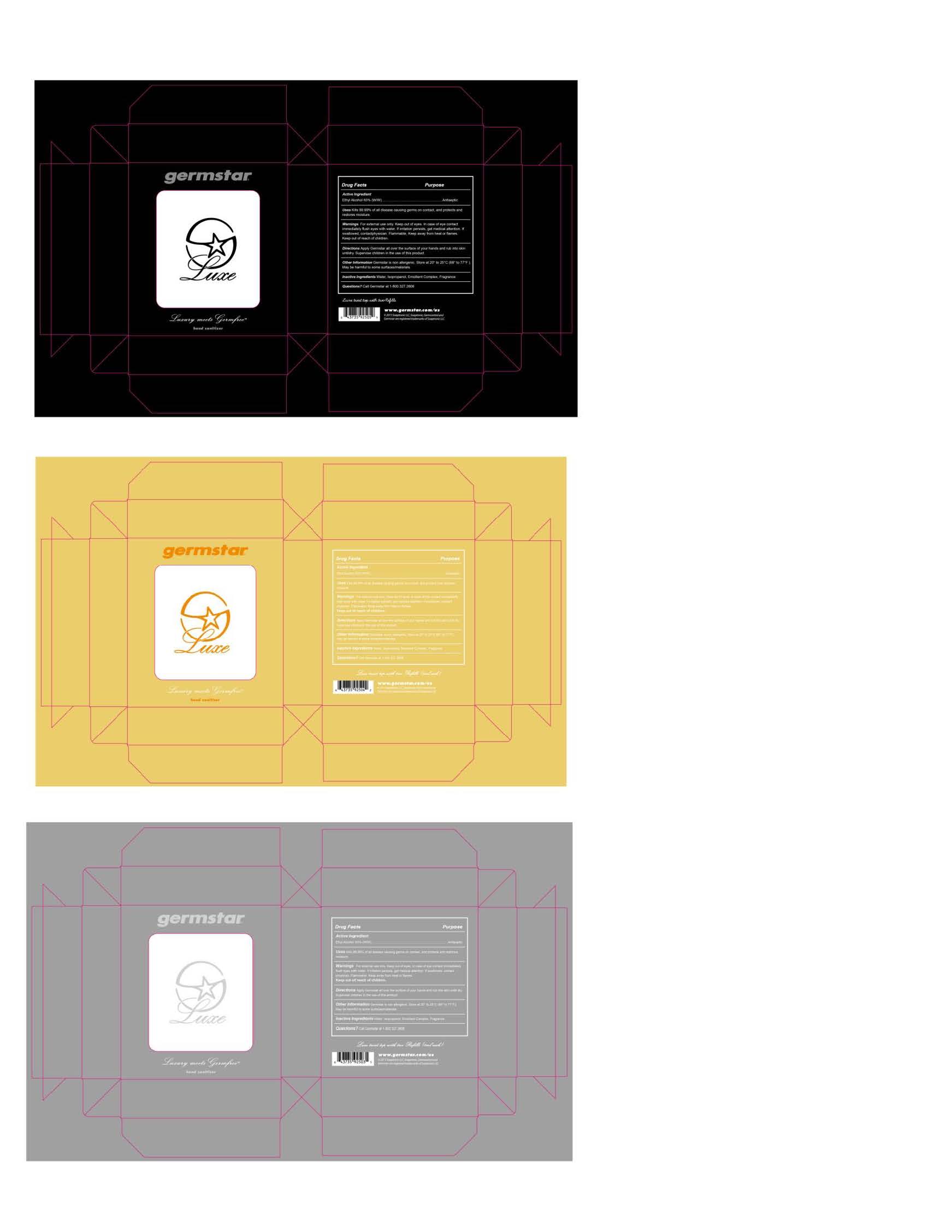 DRUG LABEL: germstarLuxe
NDC: 57915-007 | Form: SOLUTION
Manufacturer: Soaptronic, LLC
Category: otc | Type: HUMAN OTC DRUG LABEL
Date: 20250128

ACTIVE INGREDIENTS: ALCOHOL 630 g/1000 g
INACTIVE INGREDIENTS: WATER

germstarLuxe

Active ingredient

Ethyl alcohol 63% (W/W)

Purpose

Antiseptic

Uses

Kills 99.99% of all disease causing germs on contact, and protects and restores moisture.

Warnings
For external use only. Keep out of eyes. In case of eye contact immediately flush eyes with water. If irritation persists, get medical attention. If swallowed, contact physician. Flammable, keep away from heat or flames.

Keep out of reach of children.

Directions

Apply Germstar all over the surface of your hands and rub into skin until dry. Supervise children in the use of this product.

Other information

Germstar is non allergenic. Store at 20° to 25°C (68° to 77°F). May be harmful to some surfaces/materials.

Inactive ingredients

Water, Isopropanol, Emollient Complex, Fragrance

Questions?

Call Germstar at 1-800.327.2606